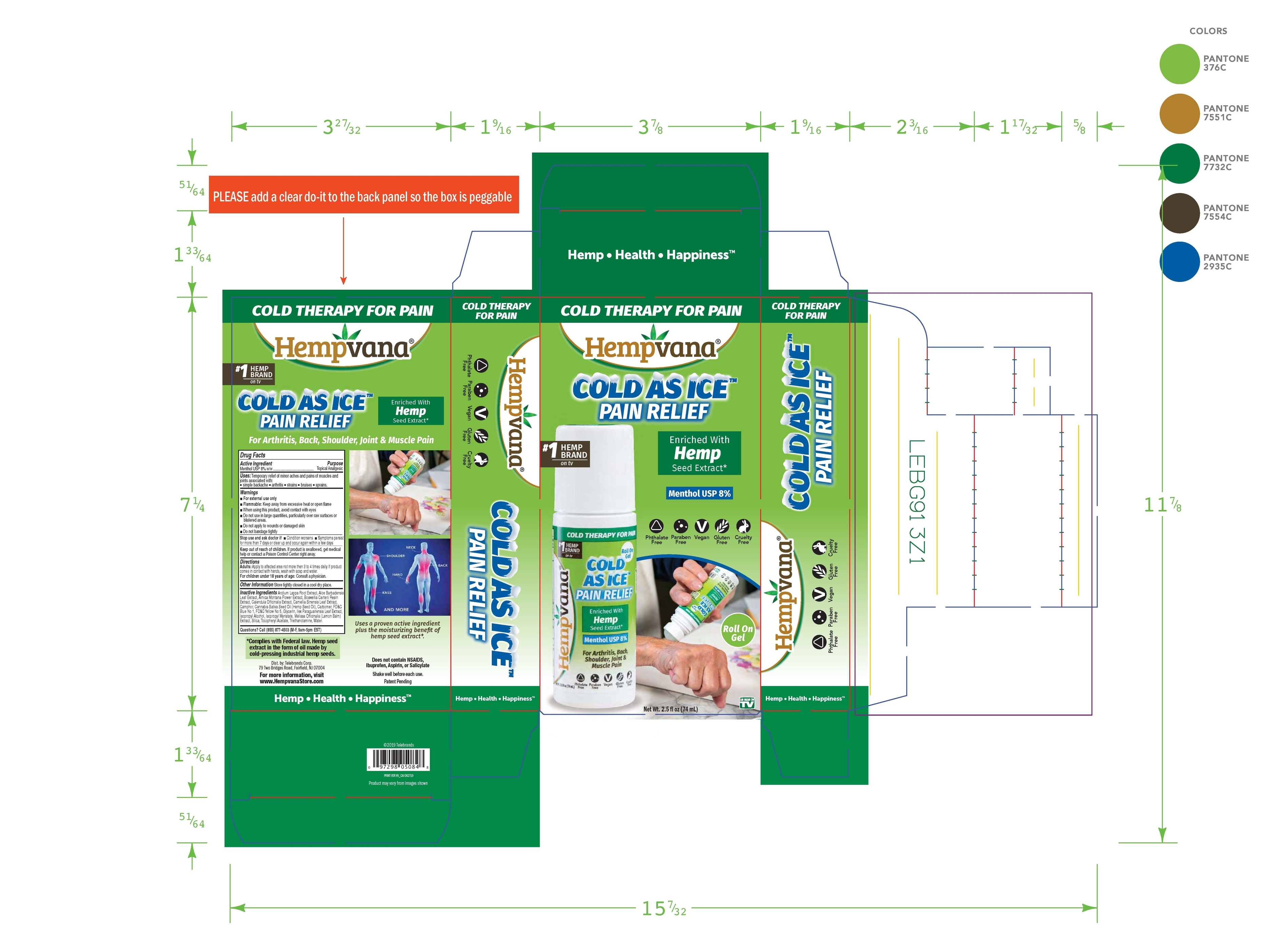 DRUG LABEL: Hempvana Cold As Ice

NDC: 73287-004 | Form: GEL
Manufacturer: Telebrands Corp
Category: otc | Type: HUMAN OTC DRUG LABEL
Date: 20251112

ACTIVE INGREDIENTS: MENTHOL 8 mg/100 mL
INACTIVE INGREDIENTS: WATER; ETHYLHEXYL STEARATE; ARCTIUM LAPPA ROOT; ALOE VERA LEAF; ILEX PARAGUARIENSIS LEAF; ARNICA MONTANA FLOWER; FRANKINCENSE; CALENDULA OFFICINALIS WHOLE; GREEN TEA LEAF; CAMPHOR (NATURAL); CANNABIS SATIVA SEED OIL; CARBOMER HOMOPOLYMER, UNSPECIFIED TYPE; FD&C BLUE NO. 1; FD&C YELLOW NO. 5; GLYCERIN; ISOPROPYL ALCOHOL; ISOPROPYL MYRISTATE; MELISSA OFFICINALIS; SILICON DIOXIDE; .ALPHA.-TOCOPHEROL ACETATE; TROLAMINE; D&C GREEN NO. 5; SODIUM HYDROXIDE; PHENOXYETHANOL

Hempvana Cold As Ice Pain Relief

Active Ingredient:

Menthol USP 8% w/w

Purpose

Menthol USP 8% w/w................Topical Analgesic

Uses

temporarily relief of minor aches and pains of muscles and joints associated with:

• simple backache • arthritis • strains • bruises • sprains

Warnings

For external use only

Flammable:Keep away from excessive heat or open flame

When using this product, avoid contact with eyes.

DO NOT USE

- Do nut use in large quantities, particularly over raw surfaces or blistered areas.
- Do not apply to wounds or damaged skin
- Do not bandage tightly

Stop use and ask a doctor if

- Condition worsens
- Symptoms persist for more than 7 days or clear up and occur again within a few days

Keep out of reach of children.If product is swallowed, get medical help or contact a Poison Control Center right away.

Directions

Adults: Apply to affected are not more than 3 to 4 times daily. If produce comes in contact with hands, wash with soap and water.

For children under 18 years of age:Consulta a physician.

STORAGE AND HANDLING

Store tightly closed in a cool dry place.

Inactive Ingredients

Arctium Lappa Root Extract, Aloe Barbadensis Leaf Extract, Arnica Montana Flower Extract, Boswellia Carterii Resin Extract, Calendula Officinalis Extract, Camellia Sinensis Leaf Extract, Camphor, Cannabis Sativa Seed Oil, Carbomer, FD&C Blue No 1, FD&C
Yellow No 5, Glycerin, Ilex Paraguariensis Leaf Extract, Isopropyl Alcohol, Isopropyl Myristate, Melissa Officinalis (Lemon Balm) Extract, Silica, Tocopheryl Acetate, Triethanolamine, Water

Questions?

Call (855) 877-4503 (M-F, 9am-5pm EST)